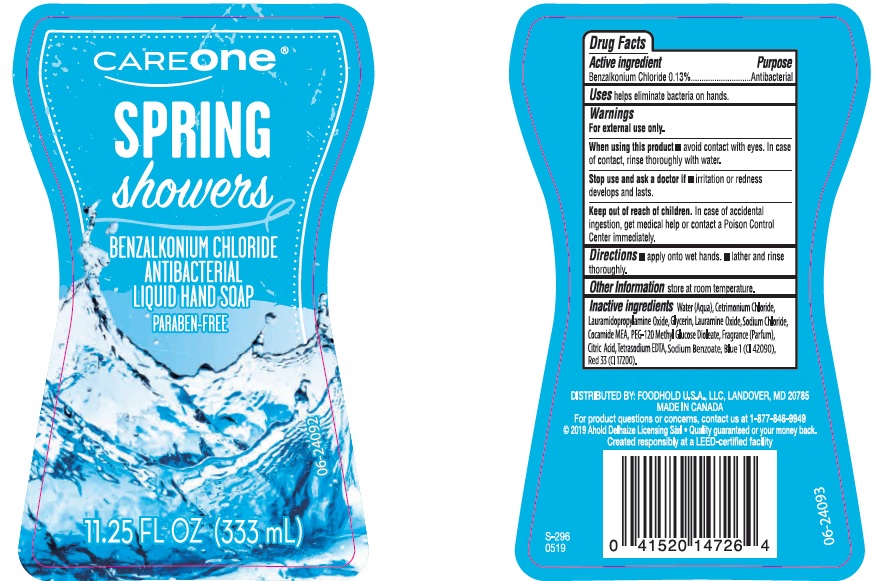 DRUG LABEL: CareOne Spring Showers Liquid Hand
NDC: 41520-307 | Form: SOAP
Manufacturer: American Sales Company
Category: otc | Type: HUMAN OTC DRUG LABEL
Date: 20190719

ACTIVE INGREDIENTS: BENZALKONIUM CHLORIDE 1.3 mg/1 mL
INACTIVE INGREDIENTS: WATER; CETRIMONIUM CHLORIDE; LAURAMIDOPROPYLAMINE OXIDE; GLYCERIN; LAURAMINE OXIDE; SODIUM CHLORIDE; COCO MONOETHANOLAMIDE; PEG-120 METHYL GLUCOSE DIOLEATE; CITRIC ACID MONOHYDRATE; EDETATE SODIUM; SODIUM BENZOATE; FD&C BLUE NO. 1; D&C RED NO. 33

Drug Facts

Active ingredient

Benzalkonium Chloride 0.13%

Purpose

Antibacterial

Uses

helps eliminate bacteria on hands.

Warnings

For external use only.

When using this product

- avoid contact with eyes. In case of contact, rinse thoroughly with water.

Sto use and ask a doctor if

- irritation or redness develops and lasts.

Keep out of reach of children.

In case of accidental ingestion, get medical help or contact a Poison Control Center immediately.

Directions

- apply onto wet hands.
- lather and rinse thoroughly.

Other information

store at room temperature.

Inactive ingredients

Water (Aqua), Cetrimonium Chloride, Lauramidopropylamine Oxide, Glycerin, Lauramine Oxide, Sodium Chloride, Cocamide MEA, PEG-120 Methyl Glucose Dioleate, Fragrance (Parfum), Citric Acid, Tetrasodium EDTA, Sodium Benzoate, Blue 1 (CI 42090), Red 33 (CI 17200).